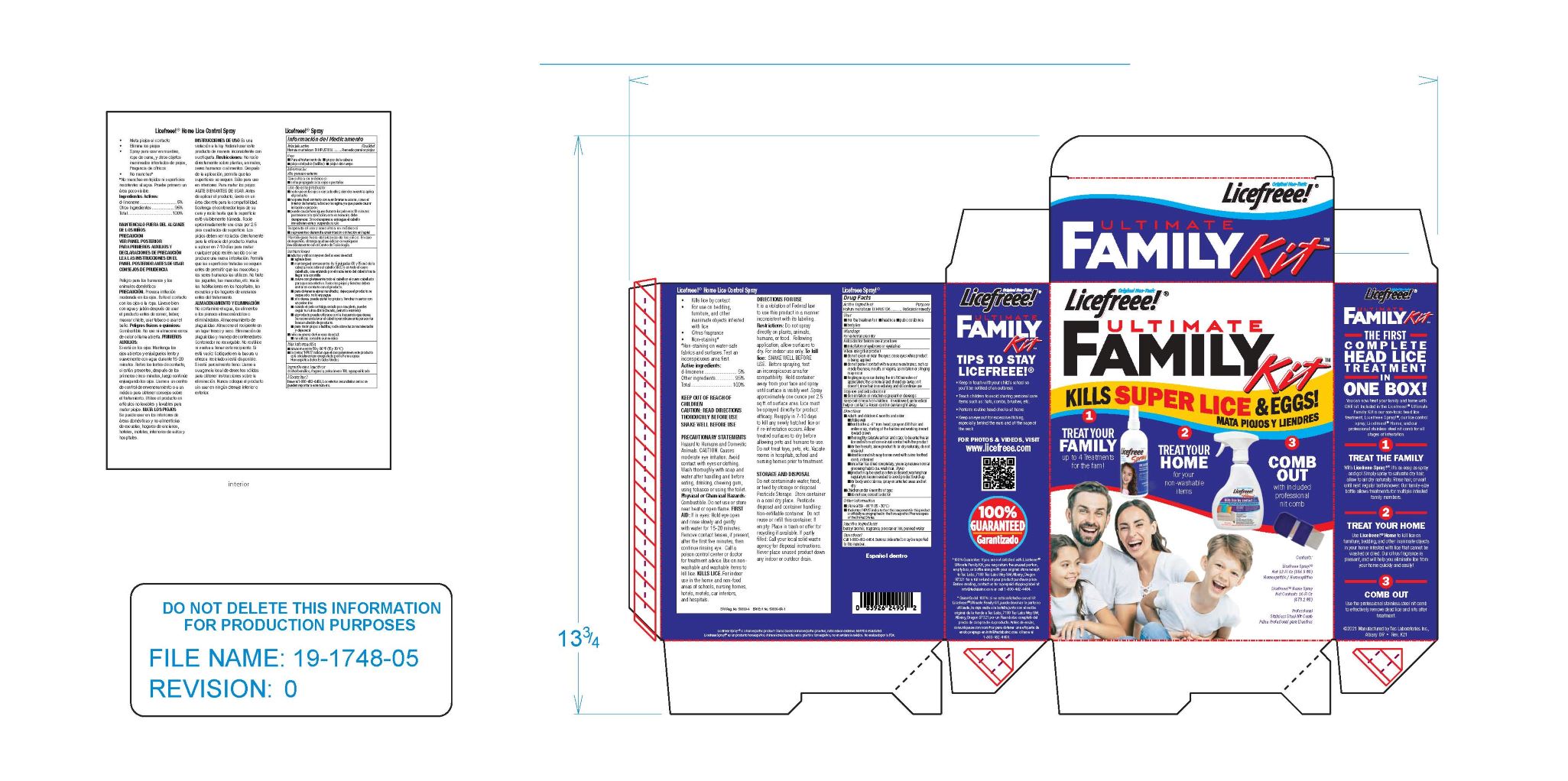 DRUG LABEL: Licefreee Ultimate Family Kit
NDC: 51879-300 | Form: KIT | Route: TOPICAL
Manufacturer: Tec Laboratories, Inc.
Category: homeopathic | Type: HUMAN OTC DRUG LABEL
Date: 20241105

ACTIVE INGREDIENTS: SODIUM CHLORIDE 1 [hp_X]/1 mL
INACTIVE INGREDIENTS: WATER; BENZYL ALCOHOL; POLOXAMER 188

LiceFreee Ultimate Family Kit

ACTIVE INGREDIENT

Natrium muriaticum 1X

PURPOSE

Peduculosis remedy

Uses

For the treatment of

- headlice
- public (crab) lice
- body lice

Warnings

For external use only

When using this product

- do not use in or near the eyes; close eyes when product is being applied
- do not permit contact with mucus membranes, such as inside the nose, mouth or vagina, as irritation or stinging may occur
- tingling may occur during the first 10 minutes of application; this is normal and should go away; if it doesn't, rinse hair immediately and discontinue use

Stop use and ask a doctor if

- skin irritation or infection is present or devleops

Keep out of reach of children

- if swallowed, get medical help or contact a Poison Control Cener right away.

Other information

Store at 59-86°F (15-30°C)

Inactive ingredients

benzyl alcohol, fragrance, poloxamer 188, purified water

Questions?

Call 1-800-482-4464. Serious side effects may be reported to this number.

Directions

- Adults and children 6 months and older:
  - shake well before each use
  - hold bottle 4-6 " from head; spray on DRY hair and entire scalp, starting at the hairline and working inward toward the crown
  - thoroughly saturate all hair and scalp; to be effective all lice and nits must come in full contact with the product
  - dead lice and nits may be removed with a fine tooth comb, if desired
  - for best results, allow product to air dry naturally, do not rinse out
  - product may be used as often as desired; washing hair regularly is recommended to aviod product build-up
  - for body and crab lice, spray on affected areas and let dry
  - Children under 6 months of age:
  - do not use; consult a doctor